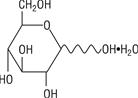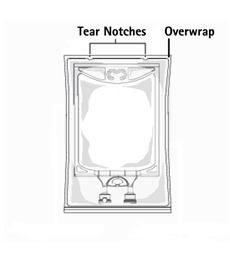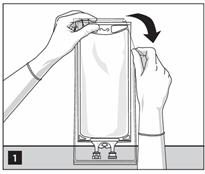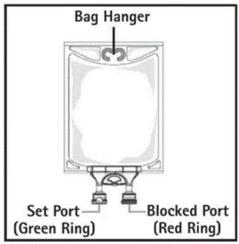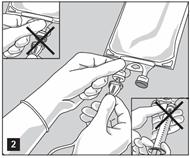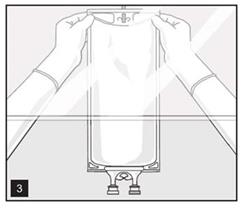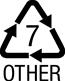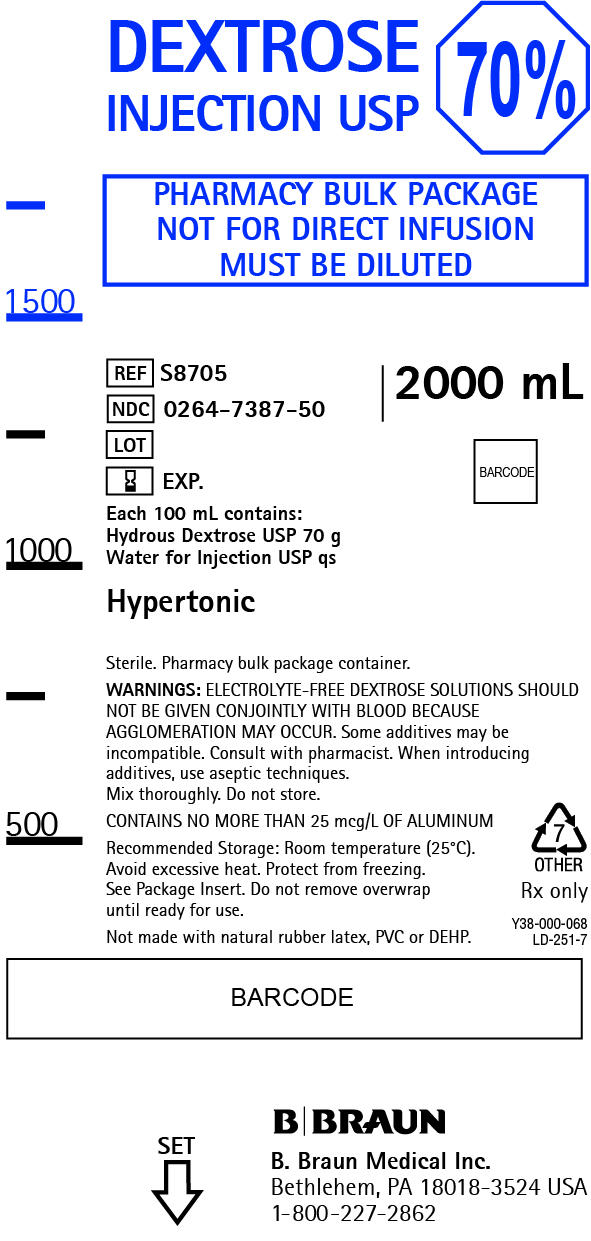 DRUG LABEL: Dextrose
NDC: 0264-7387 | Form: SOLUTION
Manufacturer: B. Braun Medical Inc.
Category: prescription | Type: HUMAN PRESCRIPTION DRUG LABEL
Date: 20241206

ACTIVE INGREDIENTS: DEXTROSE 70 g/100 mL
INACTIVE INGREDIENTS: WATER

70% Dextrose Injection USP

Concentrated Dextrose in Water

Pharmacy Bulk Package — Not For Direct Infusion.

NOTE: This solution is hypertonic — see WARNINGS and PRECAUTIONS.

DESCRIPTION

Each 100 mL of 70% Dextrose Injection USP contains:

Hydrous Dextrose USP 70 g; Water for Injection USP qs

pH: 4.0 (3.2-6.5); Calculated Osmolarity: 3532 mOsmol/liter, hypertonic.

Specific gravity 1.233 at 25°C

Calories per liter: 2380 calculated on the basis of 3.4 kcal/g of dextrose, hydrous

70% Dextrose Injection USP is sterile, nonpyrogenic and contains no bacteriostatic or antimicrobial agents. This product is intended for intravenous administration after appropriate admixture or dilution as a caloric source.

The formula of the active ingredient is:

Ingredient | Molecular Formula | Molecular Weight
Hydrous Dextrose USP |  | 198.17

Not made with natural rubber latex, PVC or DEHP.

The plastic container is made from a multilayered film specifically developed for parenteral drugs. The solution contact layer is a rubberized copolymer of ethylene and propylene. The container is nontoxic and biologically inert. The container-solution unit is a closed system and is not dependent upon entry of external air during use. The container is overwrapped to provide protection from the physical environment and to provide an additional moisture barrier when necessary.

CLINICAL PHARMACOLOGY

70% Dextrose Injection USP provides calories and is a source of water for hydration. It is capable of inducing diuresis depending on the clinical condition of the patient.

Dextrose is readily metabolized, may decrease losses of body protein and nitrogen, promotes glycogen deposition and decreases or prevents ketosis if sufficient doses are provided.

Water is an essential constituent of all body tissues and accounts for approximately 70% of total body weight. Average normal adult daily requirements range from two to three liters (1.0 to 1.5 liters each for insensible water loss by perspiration and urine production).

INDICATIONS AND USAGE

70% Dextrose Injection USP is indicated as a caloric component in a parenteral nutrition regimen. 70% Dextrose Injection USP is used with an appropriate protein (nitrogen) source in the prevention of nitrogen loss or in the treatment of negative nitrogen balance in patients where: (1) the alimentary tract cannot or should not be used, (2) gastrointestinal absorption of protein is impaired, or (3) metabolic requirements for protein are substantially increased, as with extensive burns.

CONTRAINDICATIONS

The infusion of 70% Dextrose Injection USP is contraindicated in patients having intracranial or intraspinal hemorrhage, in patients who are severely dehydrated, in patients who are anuric, and in patients in hepatic coma.

Solutions containing dextrose may be contraindicated in patients with hypersensitivity to corn products.

WARNINGS

This injection is for compounding only, not for direct infusion.

Dilute before use to a concentration which will, when administered with an amino acid (nitrogen) source, result in an appropriate calorie to gram of nitrogen ratio and which has an osmolarity consistent with the route of administration.

Unless appropriately diluted, the infusion of hypertonic dextrose injection into a peripheral vein may result in vein irritation, vein damage, and thrombosis. Strongly hypertonic nutrient solutions should only be administered through an indwelling intravenous catheter with the tip located in a large central vein such as the superior vena cava.

Use of 70% Dextrose Injection USP to prepare parenteral nutritional admixtures may be incompatible with other components, especially calcium and phosphate salts and lipid emulsions. Incompatibility of admixed components can produce precipitates which may cause particulate emboli. Use 70% Dextrose Injection USP only to prepare formulations that are known to be stable: refer to standard texts for further information.

The administration of intravenous solutions can cause fluid and/or solute overload resulting in dilution of serum electrolyte concentrations, overhydration, congested states or pulmonary edema. The risk of dilutional states is inversely proportional to the electrolyte concentration.

WARNING: 70% Dextrose Injection USP contains aluminum that may be toxic. Aluminum may reach toxic levels with prolonged parenteral administration if kidney function is impaired. Premature neonates are particularly at risk because their kidneys are immature, and they require large amounts of calcium and phosphate solutions, which contain aluminum.

Research indicates that patients with impaired kidney function, including premature neonates, who receive parenteral levels of aluminum at greater than 4 to 5 mcg/kg/day accumulate aluminum at levels associated with central nervous system and bone toxicity. Tissue loading may occur at even lower rates of administration.

Prolonged infusion of isotonic or hypotonic dextrose in water may increase the volume of extracellular fluid and cause water intoxication.

Solutions containing dextrose without electrolytes should not be administered simultaneously with blood through the same infusion set because of the possibility of agglomeration.

Excessive administration of potassium-free dextrose solutions may result in significant hypokalemia. Serum potassium levels should be maintained and potassium supplemented as required.

In very low birth weight infants, excessive or rapid administration of dextrose injection may result in increased serum osmolality and possible intracerebral hemorrhage.

PRECAUTIONS

General

This solution should be used with care in patients with hypervolemia, renal insufficiency, urinary tract obstruction, or impending or frank cardiac decompensation.

Solutions containing dextrose should be used with caution in patients with overt or known subclinical diabetes mellitus or carbohydrate intolerance for any reason.

Essential electrolytes, minerals, and vitamins should be supplied as needed.

Hypokalemia may develop during parenteral administration of hypertonic dextrose solutions. Sufficient amounts of potassium should be added to dextrose solutions administered to fasting patients with good renal function, especially those on digitalis therapy.

To minimize the risk of possible incompatibilities arising from mixing this solution with other additives that may be prescribed, the final infusate should be inspected for cloudiness or precipitation immediately after mixing, prior to administration, and periodically during administration. See WARNINGS.

Do not use plastic container in series connection.

If administration of 70% Dextrose Injection USP after admixture or dilution is controlled by a pumping device, care must be taken to discontinue pumping action before the container runs dry or air embolism may result. If administration is not controlled by a pumping device, refrain from applying excessive pressure (>300mmHg) causing distortion to the container such as wringing or twisting. Such handling could result in breakage of the container.

This solution is intended for intravenous administration after admixture or dilution using sterile equipment. When using an automated compounding device replace all disposable components as recommended by manufacturer and at least every 24 hours.

Aseptic technique is essential with the use of sterile preparations for compounding nutritional admixtures. Discard container within 4 hours of entering closure.

Administration of hypertonic dextrose and amino acid solutions via central venous catheter may be associated with complications which can be prevented or minimized by careful attention to all aspects of the procedure. This includes attention to solution preparation, administration and patient monitoring.

It is essential that a carefully prepared protocol, based upon current medical practice, be followed, preferably by an experienced team. The package insert of the protein (nitrogen) source should be consulted for dosage and all precautionary information.

Use only if solution is clear and container and seals are intact.

70% Dextrose Injection USP contains no more than 25 mcg/L of aluminum.

Laboratory Tests

Clinical evaluation and periodic laboratory determinations are necessary to monitor changes in fluid balance, electrolyte concentrations, and acid-base balance during prolonged parenteral therapy or whenever the condition of the patient warrants such evaluation. Significant deviations from normal concentrations may require tailoring of the electrolyte pattern, in these or alternative solutions.

Drug Interactions

Caution must be exercised in the administration of 70% Dextrose Injection USP to patients receiving corticosteroids or corticotropin. Some additives may be incompatible. Consult with pharmacist. When introducing additives, use aseptic techniques. Mix thoroughly. Do not store. Dispose of any unused product. See WARNINGS.

Carcinogenesis, Mutagenesis, Impairment of Fertility

Studies with Dextrose Injections USP have not been performed to evaluate carcinogenic potential, mutagenic potential or effects on fertility.

Pregnancy

There are no adequate and well controlled studies with Dextrose Injections, USP in pregnant women and animal reproduction studies have not been conducted with this drug. Therefore, it is not known whether Dextrose Injections USP can cause fetal harm when administered to a pregnant woman. Dextrose Injections USP should be given during pregnancy only if the potential benefit justifies the potential risk to the fetus.

Labor and Delivery

Intrapartum maternal intravenous infusion of glucose-containing solutions may produce maternal hyperglycemia with subsequent fetal hyperglycemia and fetal metabolic acidosis. Fetal hyperglycemia can result in increased fetal insulin levels which may result in neonatal hypoglycemia following delivery. Consider the potential risks and benefits for each specific patient before administering Dextrose Injection, USP.

Nursing Mothers

It is not known if this drug is present in human milk. Because many drugs are present in human milk, caution should be exercised when Dextrose Injections USP are administered to a nursing woman.

Pediatric Use

The use of Dextrose in pediatric patients is based on clinical practice (see DOSAGE AND ADMINISTRATION). Because of their hypertonicity, 70% Dextrose Injections must be diluted prior to administration.

Newborns – especially those born premature and with low birth weight - are at increased risk of developing hypo- or hyperglycemia and therefore need close monitoring during treatment with intravenous glucose solutions to ensure adequate glycemic control in order to avoid potential long term adverse effects. Hypoglycemia in the newborn can cause prolonged seizures, coma and brain damage. Hyperglycemia has been associated with intraventricular hemorrhage, late onset bacterial and fungal infection, retinopathy of prematurity, necrotizing enterocolitis, bronchopulmonary dysplasia, prolonged length of hospital stay, and death.

Geriatric Use

An evaluation of literature revealed no clinical experience identifying differences in responses between the elderly and younger patients. In general, dose selection for an elderly patient should be cautious, usually starting at the low end of the dosing range, reflecting the greater frequency of decreased hepatic, renal, or cardiac function, and of concomitant disease or other drug therapy.

This drug is known to be substantially excreted by the kidney, and the risk of toxic reactions to this drug may be greater in patients with impaired renal function. Because elderly patients are more likely to have decreased renal function, care should be taken in dose selection, and it may be useful to monitor renal function.

See WARNINGS.

ADVERSE REACTIONS

Reactions which may occur because of the solution or the technique of administration include febrile response, infection at the site of injection, venous thrombosis or phlebitis extending from the site of injection, extravasation and hypervolemia. Incompatibility of admixed components can produce precipitates which may cause particulate emboli.

Hyperosmolar syndrome, resulting from excessively rapid administration of concentrated dextrose may cause hypovolemia, dehydration, mental confusion and/or loss of consciousness. Too rapid infusion of hypertonic solutions may cause local pain and venous irritation. Rate of administration should be adjusted according to tolerance. Use of the largest peripheral vein and a small bore needle is recommended. (See DOSAGE AND ADMINISTRATION.)

Hypersensitivity reactions, including anaphylaxis and chills.

If an adverse reaction does occur, discontinue the infusion, evaluate the patient, institute appropriate therapeutic countermeasures, and save the remainder of the fluid for examination if deemed necessary.

OVERDOSAGE

In the event of a fluid or solute overload during parenteral therapy, reevaluate the patient’s condition and institute appropriate corrective treatment.

DOSAGE AND ADMINISTRATION

This solution is for intravenous use only after admixture or dilution.

70% Dextrose Injection USP is designed for use with automated compounding devices for preparing intravenous nutritional admixtures or for the filling of empty sterile syringes. Dosages will be in accordance with the recommendation of the prescribing physician. 70% Dextrose Injection USP is not intended for direct infusion. Admixtures should be made by, or under the direction of, a pharmacist using strict aseptic technique under a laminar flow hood. Compounded admixtures may be stored under refrigeration for up to 24 hours. Administration of admixtures should be completed within 24 hours after removal from refrigeration.

Dosage is to be directed by a physician and is dependent upon age, weight, clinical condition of the patient and laboratory determinations. Frequent laboratory determinations and clinical evaluation are essential to monitor changes in blood glucose and electrolyte concentrations, and fluid and electrolyte balance during prolonged parenteral therapy.

Fluid Administration should be based on calculated maintenance or replacement fluid requirements for each patient.

Pediatric Use

The dosage selection and constant infusion rate of intravenous dextrose must be selected with caution in pediatric patients, particularly neonates and low birth weight infants, because of the increased risk of hyperglycemia/hypoglycemia. Frequent monitoring of serum glucose concentrations is required when dextrose is prescribed to pediatric patients, particularly neonates and low birth weight infants. The infusion rate and volume depends on the age, weight, clinical and metabolic conditions of the patient, concomitant therapy and should be determined by the consulting physician experienced in pediatric intravenous fluid therapy.

Directions for Use of Pharmacy Bulk Package Container

Parenteral drug products should be inspected visually for particulate matter and discoloration prior to administration or admixture and final infusate should be inspected for cloudiness or precipitation immediately after mixing, prior to administration, and periodically during administration, whenever solution and container permit. Use of a final filter is recommended during administration of all parenteral solutions where possible.

70% Dextrose Injection USP in the Pharmacy Bulk Package is intended for use in the preparation of sterile, intravenous admixtures.

Refer to standard texts and guidelines on the preparation of parenteral nutritional admixtures.

When compounding admixtures, use aseptic technique. Mix thoroughly.

Do not store any unused portion of 70% Dextrose Injection USP.

TO OPEN:

1. Inspect overwrap. Do not use if overwrap has been damaged.
2. Do not use unless solution is clear and closure is intact.
3. Tear overwrap starting from the tear notches. (Figure 1)
4. Inspect the container for minute leaks by squeezing inner bag firmly. If leaks are found, discard the bag as sterility may be impaired.
5. For compounding only. Do not use for direct infusion.
  PREPARATION FOR ADMIXING
  Note: Important Admixing Information

- The Pharmacy Bulk Package is to be used only in a suitable work area such as a laminar air flow hood (or an equivalent clean air compounding area).
- The contents are restricted to the preparation of admixtures for infusion or, through a sterile transfer device, for the filling of empty sterile syringes.
- Additives may be incompatible with the fluid withdrawn from this container. When compounding admixtures, use aseptic technique, mix thoroughly and do not store.
- Parenteral drug products should be inspected visually for particulate matter and discoloration prior to administration whenever solution container permits. (see PRECAUTIONS, General)

1. Do not use/penetrate blocked port (see Figure 2, left upper corner).
2. Remove aluminum foil of set port at the bottom of container.
3. Attach suitable transfer device or compounding set (Figure 2). Refer to complete directions accompanying device.
4. Hang bag on suitable fixture (Figure 3).
5. Once container closure has been penetrated, withdrawal of content should be completed within 4 hours.

HOW SUPPLIED

70% Dextrose Injection USP is supplied in 2000 mL Pharmacy Bulk Package containers packaged 4 per case.

NDC REF SIZE
0264-7387-50 S8705 2000 mL

Exposure of pharmaceutical products to heat should be minimized. Avoid excessive heat. Protect from freezing. It is recommended that the product be stored at room temperature (25°C); however, brief exposure up to 40°C does not adversely affect the product.

Rx only

Revised: May 2019

B. Braun Medical Inc.
Bethlehem, PA 18018-3524 USA
1-800-227-2862
Y36-002-997 LD-355-4

PRINCIPAL DISPLAY PANEL

70% DEXTROSE
INJECTION USP

PHARMACY BULK PACKAGE
NOT FOR DIRECT INFUSION
MUST BE DILUTED

REF S8705
NDC 0264-7387-50
LOT
EXP.

2000 mL

Each 100 mL contains:
Hydrous Dextrose USP 70 g
Water for Injection USP qs

Hypertonic

Sterile. Pharmacy bulk package container.

WARNINGS: ELECTROLYTE-FREE DEXTROSE SOLUTIONS SHOULD
NOT BE GIVEN CONJOINTLY WITH BLOOD BECAUSE
AGGLOMERATION MAY OCCUR. Some additives may be
incompatible. Consult with pharmacist. When introducing
additives, use aseptic techniques.
Mix thoroughly. Do not store.

CONTAINS NO MORE THAN 25 mcg/L OF ALUMINUM

Recommended Storage: Room temperature (25°C).
Avoid excessive heat. Protect from freezing.
See Package Insert. Do not remove overwrap
until ready for use.

Not made with natural rubber latex, PVC or DEHP.

Rx only

Y38-000-068 LD-251-7

B. Braun Medical Inc.
Bethlehem, PA 18018-3524 USA
1-800-227-2862
SET

70% Dextrose 2000mL Container Label